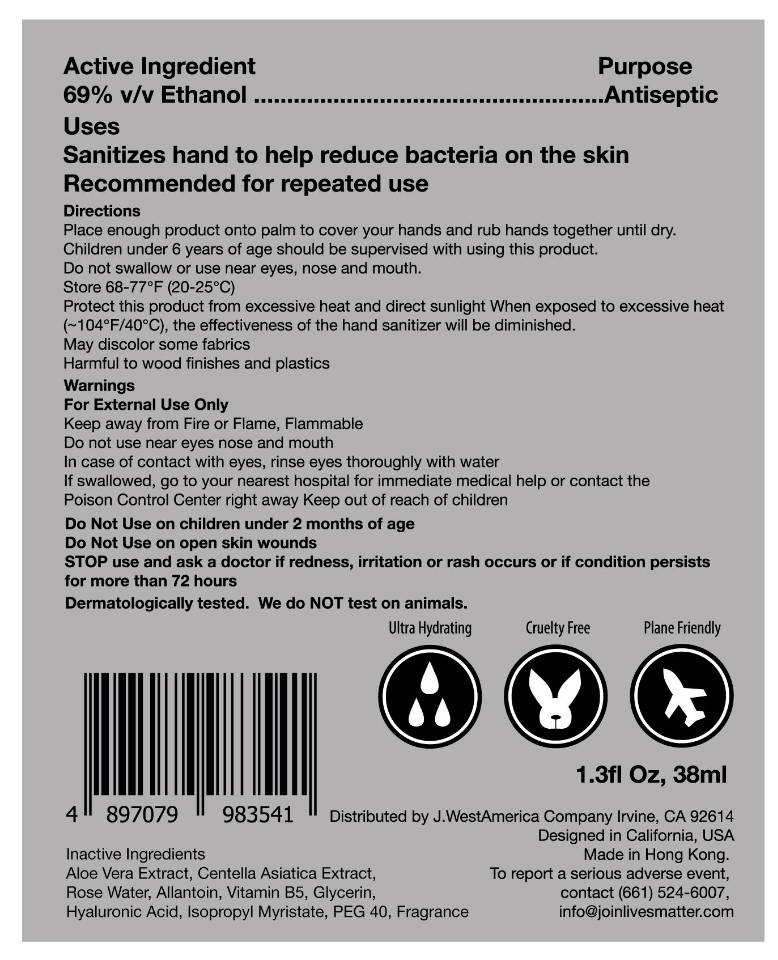 DRUG LABEL: Hand Sanitizer by Medpanol
NDC: 77606-103 | Form: LIQUID
Manufacturer: Sun Hing Petrochemical Company Limited
Category: otc | Type: HUMAN OTC DRUG LABEL
Date: 20200909

ACTIVE INGREDIENTS: ALCOHOL 26.22 mL/38 mL
INACTIVE INGREDIENTS: PEG-40 SORBITAN DIISOSTEARATE; ALLANTOIN; PANTOTHENIC ACID, (+/-)-; HYALURONIC ACID; ISOPROPYL MYRISTATE; SEDUM ROSEUM WHOLE; ALOE VERA LEAF; GLYCERIN; WATER; P-ANISIC ACID; CENTELLA ASIATICA

SunHing, Medpanol Hand Sanitizer, Ethanol 69% v/v, Liquid, Bottle-Spray, 38mL

Active Ingredient

Ethanol 69% v/v. Purpose: Antiseptic

Purpose

Antiseptic

Uses

Sanitizes hand to help reduce bacteria on the skin

Recommended for repeated use

Warnings

For external use only

Keep away from Fire or Flame, Flammable

Do Not Use on children under 2 months of age

Do Not Use on open skin wounds

Do not use near eyes nose and mouth

In case of contact with eyes, rinse eyes thoroughly with water

STOP use and ask a doctor if redness, irritation or rash occurs or if condition persists for more than 72 hours

Keep out of reach of children

If swallowed, go to your nearest hospital for immediate medical help or contact the Posion Control Center right away

Directions

Place enough product onto palm to cover your hands and rub hands together until dry.
Children under 6 years of age should be supervised with using this product.

Do not swallow or use near eyes, nose and mouth.

STORAGE AND HANDLING

Store 68-77℉ (20-25℃)

Protect this product from excessive heat and direct sunlight

When exposed to excessive heat 104℉/40℃, the effectiveness of the hand sanitizer will be diminished.

May discolor some fabrics

Harmful to wood finishes and plastics

Inactive ingredients

Aloe Vera Extract, Centella Asiatica Extract, Rose Water, Allantoin, Vitamin B5, Glycerin, Hyaluronic Acid, Isopropyl Myristate, PEG 40, Fragrance, Water